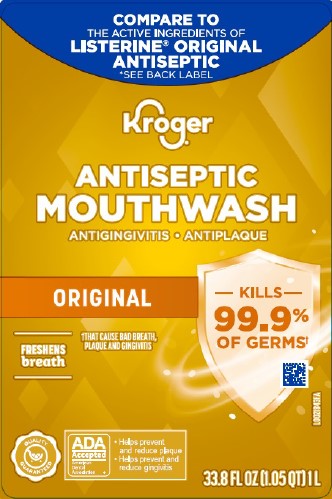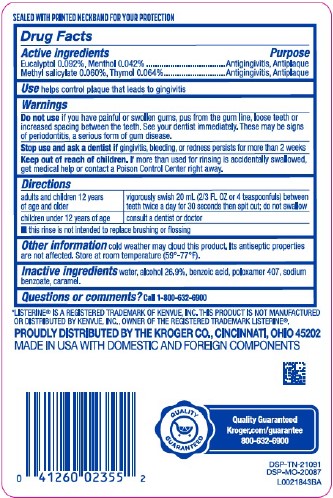 DRUG LABEL: Antiseptic Mouth Rinse
NDC: 30142-318 | Form: MOUTHWASH
Manufacturer: The Kroger Co.
Category: otc | Type: HUMAN OTC DRUG LABEL
Date: 20260227

ACTIVE INGREDIENTS: EUCALYPTOL 0.92 mg/1 mL; MENTHOL 0.42 mg/1 mL; METHYL SALICYLATE 0.6 mg/1 mL; THYMOL 0.64 mg/1 mL
INACTIVE INGREDIENTS: WATER; ALCOHOL; BENZOIC ACID; POLOXAMER 407; SODIUM BENZOATE; CARAMEL

Kroger 318.003/318AH-AI
Antiseptic Mouthrinse

Tamper Evident Statement

SEALED WITH PRINTED NECKBAND FOR YOUR PROTECTION

Active ingredients

Eucalyptol 0.092%

Menthol 0.042%

Methyl salicylate 0.060%

Thymol 0.064%

Purpose

Antigingivitis, Antiplaque

Use

helps control plaque that leads to gingivitis

Warnings

for this product

Do not use

if you have painful or swollen gums, pus from the gum line, loose teeth or increased spacing between the teeth. See your dentist immediately. These may be signs of periodtitis, a serious form of gum disease.

Stop use and ask a dentist

gingivitis, bleeding, or redness persists for more than 2 weeks

Keep out of reach of children.

If more than used for rinsing is accidentally swallowed, get medical help or contact a Poison Control Center right away.

Directions

adults and children 12 years of age and older - vigorously swish 20 mL (2/3 FL OZ or 4 teaspoonfuls) between teeth twice a day for 30 seconds then spit out; do not swallow

children under 12 years of age - consult a dentist or doctor

- this rinse is not intended to replace brushing or flossing

Other information

cold weather may cloud this product. Its antiseptic properties are not affected. Store at room temperature (59°-77°F).

Inactive ingredients

water, alcohol 26.9%, benzoic acid, poloxamer 407, sodium benzoate, caramel

Questions or comments?

Call 1-800-632-6900

Disclaimer

*LISTERINEIS A REGISTERED TRADEMARK OF KENVUE, INC. THIS PRODUCT IN NOT MANUFACTURED OR DISTRIBUTED BY KENVUE, INC., OWNER OF THE REGISTERED TRADEMARK LISTERINE®.

Adverse Reactions

PROUDLY DISTRIBUTED BY THE KROGER CO., CINCINNATI, OHIO 45202

MADE IN USA WITH DOMESTIC AND FOREIGN COMPONENTS

QUALITY GUARANTEED

Kroger.com/guarantee

800-632-6900

DSP-TN-21091

DSP-MO-20087

Principal display panel

COMPARE TO THE ACTIVE INGREDIENTS OF LISTERINE®ORIGINAL ANTISEPTIC

*See Back Label

KROGER®

ANTISEPTIC

MOUTHWASH

ANTIGINGIVITIS • ANTIPLAQUE

ORIGINAL

KILLS 99.9% OF GERMS†

FRESHENS breath

†THAT CAUSE BAD BREATH, PLAQUE AND GINGIVITIS

QUALITY GUARANTEED

ADA Accepted

American Dental Association

- Helps prevent and reduce plaque
- Helps prevent and reduce gingivitis

33.8 FL OZ (1.05 QT) 1 L